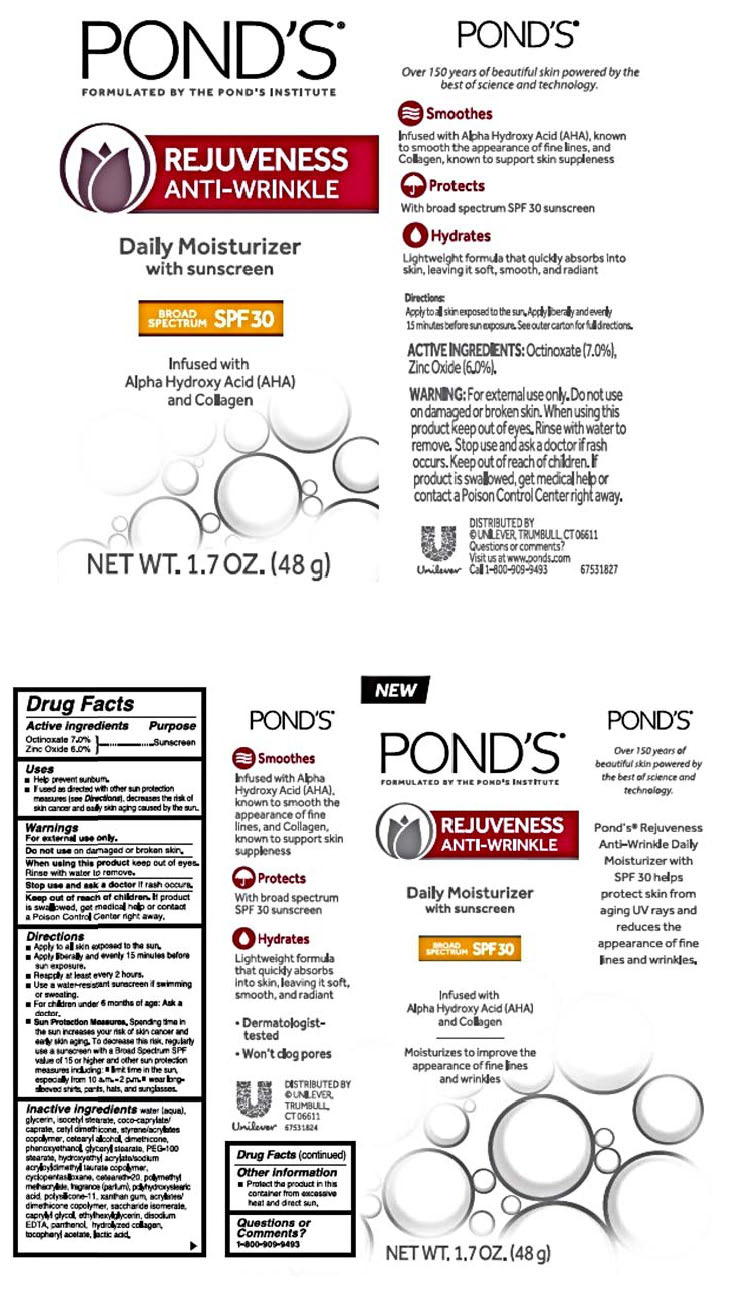 DRUG LABEL: Ponds
NDC: 64942-1584 | Form: CREAM
Manufacturer: CONOPCO Inc. d/b/a Unilever
Category: otc | Type: HUMAN OTC DRUG LABEL
Date: 20241107

ACTIVE INGREDIENTS: ZINC OXIDE 6 g/100 g; OCTINOXATE 7 g/100 g
INACTIVE INGREDIENTS: HYDROXYETHYL ACRYLATE/SODIUM ACRYLOYLDIMETHYL TAURATE COPOLYMER (100000 MPA.S AT 1.5%); CYCLOMETHICONE 5; POLYHYDROXYSTEARIC ACID STEARATE; POLY(METHYL METHACRYLATE; 450000 MW); DIMETHICONE/VINYL DIMETHICONE CROSSPOLYMER (SOFT PARTICLE); SACCHARIDE ISOMERATE; PANTHENOL; LACTIC ACID; CETOSTEARYL ALCOHOL; CAPRYLYL GLYCOL; ETHYLHEXYLGLYCERIN; COCO-CAPRYLATE/CAPRATE; GLYCERIN; CETYL DIMETHICONE 150; WATER; PEG-100 STEARATE; DIMETHICONE; .ALPHA.-TOCOPHEROL ACETATE; GLYCERYL MONOSTEARATE; POLYOXYL 20 CETOSTEARYL ETHER; XANTHAN GUM; STYRENE/ACRYLAMIDE COPOLYMER (500000 MW); ISOCETYL STEARATE; PHENOXYETHANOL; EDETATE DISODIUM

Pond's Rejuveness Anti-Wrinkle Daily Moisturizer with Sunscreen SPF 30

POND'S REJUVENESS ANTI-WRINKLE DAILY MOISTURIZER WITH SUNSCREEN SPF 30 - octinate, zinc oxide cream

Pond's Rejuveness Anti-Wrinkle Daily Moisturizer with Sunscreen SPF 30

Drug Facts

Active Ingredients
Octinoxate (7.0%)
Zinc Oxide (6.0%)

Purpose

Sunscreen

Uses

· helps prevent sunburn
· if used as directed with other sun protection measures (see Directions), decreases the risk of skin cancer and early skin aging caused by the sun

Warnings

• For external use only.
• Do not use on damaged or broken skin.
• When using this product keep out of eyes. Rinse with water to remove.
• Stop use and ask a doctor if rash occurs.

• Keep out of reach of children.

If swallowed, get medical help or contact a Poison Control Center right away.

Directions

• Apply to all skin exposed to the sun.
• Apply liberally and evenly 15 minutes before sun exposure.
• Reapply at least every 2 hours.
• Use a water-resistant sunscreen if swimming or sweating.
• For children under 6 months of age: Ask a doctor.
• Sun Protection Measures. Spending time in the sun increases your risk of skin cancer and early skin aging. To decrease this risk, regularly use a sunscreen with a Broad Spectrum SPF value of 15 or higher and other sun proection measures including:
• Limit time in the sun, especially from 10 a.m. - 2 p.m.
• Wear long-sleeved shirts, pants, hats, and sunglasses.

Inactive ingredients

Water (Aqua), Glycerin, Styrene/Acrylates Copolymer, Isocetyl Stearate, Coco-Caprylate/Caprate, Cetyl Dimethicone, Cetearyl Alcohol, Dimethicone, Phenoxyethanol, Glyceryl Stearate, PEG-100 Stearate, Hydroxyethyl Acrylate/Sodium Acryloyldimethyl Taurate Copolymer, Cyclopentasiloxane, Ceteareth-20, Polymethyl Methacrylate, Fragrance (Parfum), Polyhydroxystearic Acid, Polysilicone-11, Xanthan Gum, Acrylates/Dimethicone Copolymer, Saccharide Isomerate, Caprylyl Glycol, Ethylhexylglycerin, Disodium EDTA, Panthenol, Hydrolyzed Collagen, Tocopheryl Acetate, Lactic acid.

Questions?

Call toll-free 1-800-909-9493

OTHER SAFETY INFORMATION

• Protect the product in this container from excesive heat and direct sun.

Smoothes
Infused with Alpha Hydroxy Acids (AHAs), known to smooth the appearance of fine lines, and Collagen, known to support skin suppleness
Protects
With broad spectrum SPF 30 sunscreen
Hydrates
Lightweight formula that quickly absorbs into skin, leaving it soft, smooth, and radiant
• Dermatologist-tested
• Won't clog pores